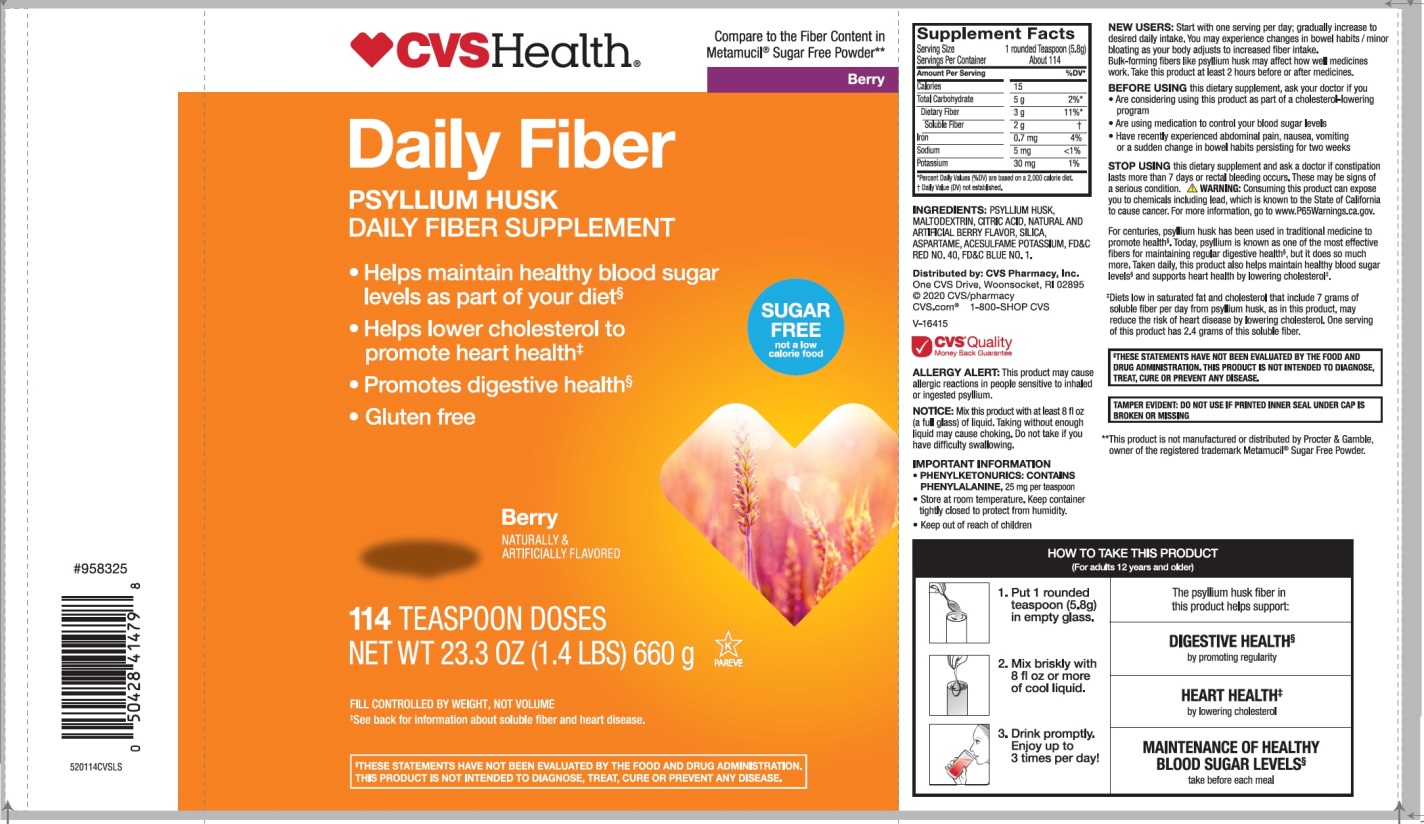 DRUG LABEL: CVS Health Natural Daily Fiber Sugar Free
NDC: 59779-934 | Form: POWDER
Manufacturer: CVS Pharmacy,Inc.
Category: otc | Type: HUMAN OTC DRUG LABEL
Date: 20200828

ACTIVE INGREDIENTS: PSYLLIUM HUSK 3.4 g/5.78 g
INACTIVE INGREDIENTS: ACESULFAME POTASSIUM; ASPARTAME; ANHYDROUS CITRIC ACID; FD&C BLUE NO. 1; FD&C RED NO. 40; MALTODEXTRIN; SILICON DIOXIDE

CVS Health™ Natural Daily Fiber Smooth Dissolving 100% Natural Psyllium Husk Berry Flavor Sugar free 114 Teaspoon Doses

Drug Facts

Active ingredient: (in each TEASPOON)

Psyllium husk approximately 3.4 g

Purpose

Fiber therapy for regularity

Uses:

- for relief of occasional constipation (irregularity)

Warnings:

Choking:

Taking this product without adequate fluid may cause it to swell and block your throat or esophagus and may cause choking. Do not take this product if you have difficulty in swallowing. If you experience chest pain, vomiting, or difficulty in swallowing or breathing after taking this product, seek immediate medical attention.

Allergy alert:

This product may cause allergic reaction in people sensitive to inhaled or ingested psyllium.

Ask a doctor before use if you have

- a sudden change in bowel habits persisting for 2 weeks
- abdominal pain, nausea or vomiting

Stop use and ask a doctor if

- constipation lasts more than 7 days
- rectal bleeding occurs

These may be signs of a serious condition.

Keep out of reach of children. In case of overdose, get medical help or contact a Poison Control Center right away at 1-800-222-1222.

Directions:

Put one dose into an empty glass. Mix this product (child or adult dose) with at least 8 ounces (a full glass) of water or other fluid. Taking this product without enough liquid may cause choking. See choking warning. Stir briskly and drink promptly. If mixture thickens, add more liquid and stir.

Adults 12 years & older: | 1 rounded TEASPOON in 8 oz of liquid at the first sign of irregularity. Can be taken up to 3 times daily. Generally produces effect in 12-72 hours.
6 – 11 yrs : | ½ adult dose in 8 oz of liquid, up to 3 times daily
Under 6 yrs: | Consult a doctor

Bulk forming fibers like psyllium husk may affect how well other medicines work. If you are taking a prescription medicine by mouth, take this product at least 2 hours before or 2 hours after the prescribed medicine. As your body adjusts to increased fiber intake, you may experience changes in bowel habits or minor bloating.

New Users

Start with 1 serving per day; gradually increased to desired daily intake. You may initially experience changes in bowel habits or minor bloating, as your body adjusts to increased fiber intake.

Other information:

- each teaspoon contains: potassium 35 mg; sodium 5 mg
- PHENYLKETONURICS: CONTAINS PHENYLALANINE, 25 mg per teaspoon
- store at room temperature tightly closed to protect from humidity
- Keep out of reach of children
- do not use if printed inner seal is broken or missing
- contains a 100% natural, therapeutic fiber

Inactive ingredients:

Acesulfame potassium, aspartame, citric acid, FD&C Blue 1, FD&C Red 40,maltodextrin, natural and artificial berry flavors, silica.

Questions or comments?

1-866-467-2748

PRINCIPAL DISPLAY PANEL

CVS Health™

Compare to the active ingredient in Metamucil® 4 in 1 MultiHealth Fiber*

Berry

NDC 59779-934-11

Natural Daily Fiber

100% NATURAL PSYLLIUM HUSK

MULTI-BENEFIT DAILY FIBER SUPPLEMENT

THERAPY FOR REGULARITY

- Helps you feel less hungry between meals**
- Helps maintain healthy blood sugar levels as part of your diet**
- Helps lower cholesterol to promote heart health†
- Promotes digestive health**
- Gluten free

SUGAR FREE not a low calorie food

Berry

NATURALLY & ARTIFICIALLY FLAVORED

114 TEASPOONS‡

NET WT 23.3 OZ (1.4 LB) (660g)

FILL CONTROLLED BY WEIGHT, NOT VOLUME

†See back for information about soluble fiber and heart disease.

‡Serving size varies. See DIRECTIONS on back panel for more information

GLUTEN FREE

If you have specific dietary needs, you should consult your doctor before consuming this product.

This product has a low glycemic index, a measure of the effect of dietary carbohydrates on blood sugar levels.

DO NOT USE IF PRINTED INNER SEAL IS BROKEN OR MISSING

**These statements have not been evaluated by the Food and Drug Administration. This product is not intended to diagnose, treat, cure or prevent any disease.

*This product is not manufactured or distributed by Procter & Gamble, the distributor of Metamucil®.

4 in 1 MultiHealth Fiber*

Distributed by: CVS Pharmacy, Inc.

One CVS Drive,

Woonsocket, RI 02895

© 2020 CVS/pharmacy

CVS.com® 1-800-SHOP CVS

CVS® Quality

Money Back Guarantee